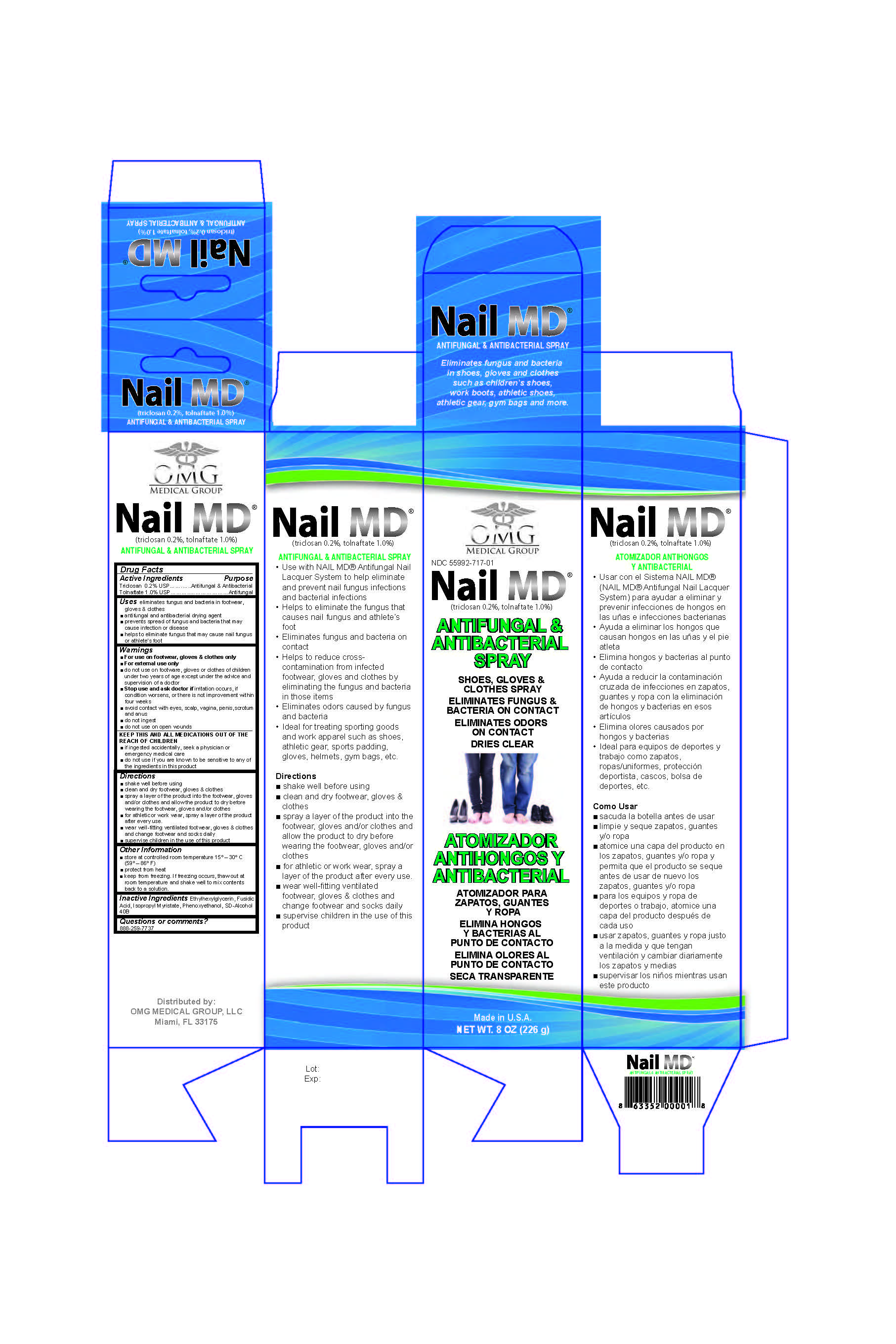 DRUG LABEL: Nail MD
NDC: 55992-717 | Form: SPRAY
Manufacturer: OMG Medical Group, LLC
Category: otc | Type: HUMAN OTC DRUG LABEL
Date: 20140115

ACTIVE INGREDIENTS: Triclosan 20 mg/1 mg; TOLNAFTATE 100 mg/1 mg
INACTIVE INGREDIENTS: ETHYLHEXYLGLYCERIN; FUSIDIC ACID; ISOPROPYL MYRISTATE; PHENOXYETHANOL; ALCOHOL

Nail MD

do not use on children under two years of age except under the advce and supervision of a doctor

stop use and ask a doctor if irritation occurs, if condition worsesn, or there is not improvement within four weeks

for external use only

avoid contact with eyes, scalp, vagina, penis, scrotum and anus

do not ingest

do not use on open wounds

in case of accidental ingestion, contact a physician, emergency medical

do not use if you are known to be sensitive to any of the ingredients in this product

INACTIVE INGREDIENT

aqua (deionized water), biotin, dimethyl sulfone (msm), ethyoxydiglycol, ethylhexylglycerin, hydrolyzed keratin proteins, hydroxyethylcellulose, phenoxyethanol, polysorbate 20, sd alcohol 40B

ACTIVE INGREDIENT

miconazole nitrate 2% USP

PURPOSE

Topical antifungal

uses

antifungal drying agent

is indicated for candida albicans, trichophyton rubrum, malassezia furfur, trichophyton mentagrophytes

as well as somegram postivie bacteria

lessens the signs of nail dystophy (nail damage caused by trauma or diseas such as fungal infection)

directions

shake well before using

clean and dry affected areas

apply twice per day or as recommended by your doctor

with the brush applicator a thin layer of the product making sure to coat both the nail and cuticle completely

other information

store at controlled room temperature 15-30 degrees celsius (59-86 degrees farenhight)

protect from heat

keep from freezing, if freezing occurs, thaw out at room temperature and shake well to mix contents back to a solution

KEEP OUT OF REACH OF CHILDREN

keep this and all medications out of the reach of children